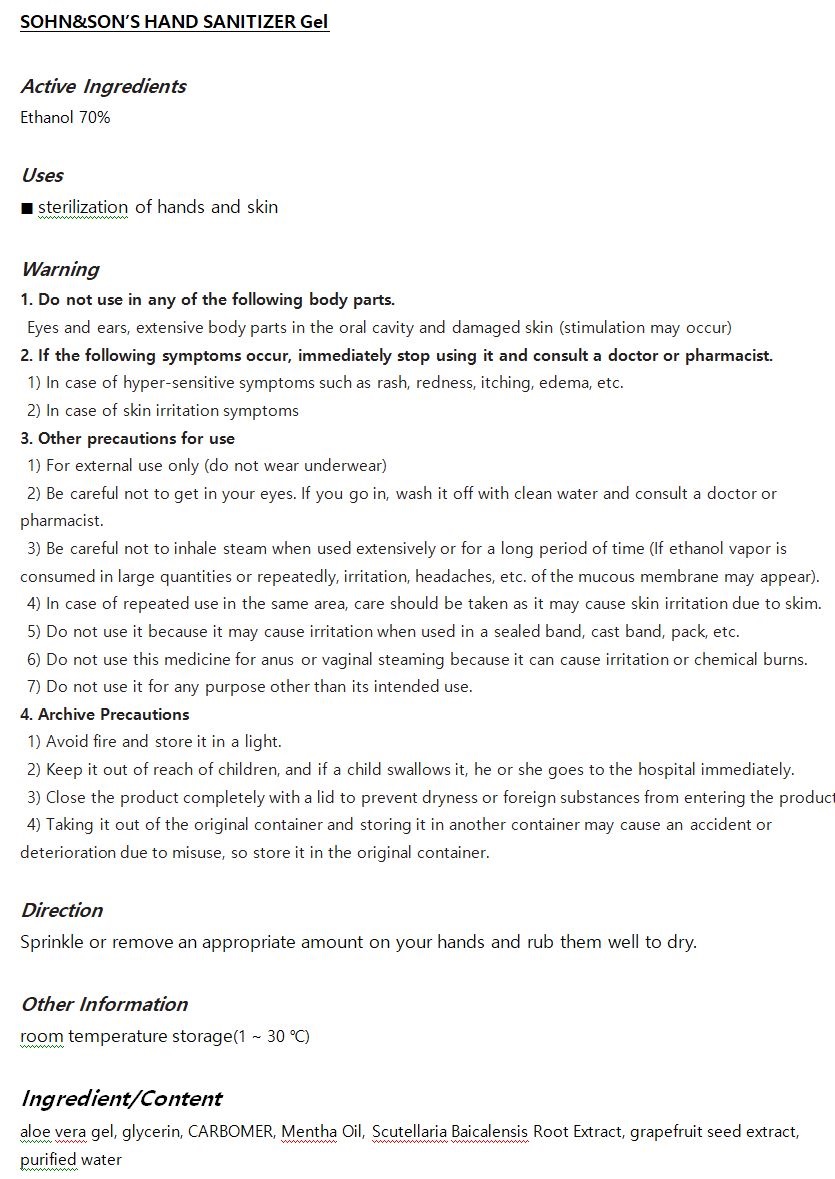 DRUG LABEL: SOHN SONS HAND SANITIZER gel
NDC: 71583-1004 | Form: GEL
Manufacturer: B.N.trinity Co.,Ltd
Category: otc | Type: HUMAN OTC DRUG LABEL
Date: 20200718

ACTIVE INGREDIENTS: ALCOHOL 70 mL/100 mL
INACTIVE INGREDIENTS: GRAPEFRUIT SEED OIL; WATER; CARBOMER 940; ALOE VERA LEAF

Drug Facts

ACTIVE INGREDIENT

ethanol

PURPOSE

■ sterilization of hands and skin

KEEP OUT OF REACH OF THE CHILDREN

WARNINGS

■ Flammable. Keep away from fire or flame.

■ For external use only.

■ Do not use in eyes.

■ lf swallowed, get medical help promptly.

■ Stop use, ask doctor lf irritation occurs.

■ Keep out of reach of children.

DOSAGE AND ADMINISTRATION

for external use only

INACTIVE INGREDIENT

aloe vera gel, glycerin, CARBOMER, Mentha Oil, Scutellaria Baicalensis Root Extract, grapefruit seed extract,

purified water

INDICATIONS AND USAGE

wet hands thoroughly with product and allow to dry without wiping

for children under 6, use only under adult supervision

not recommended for infants